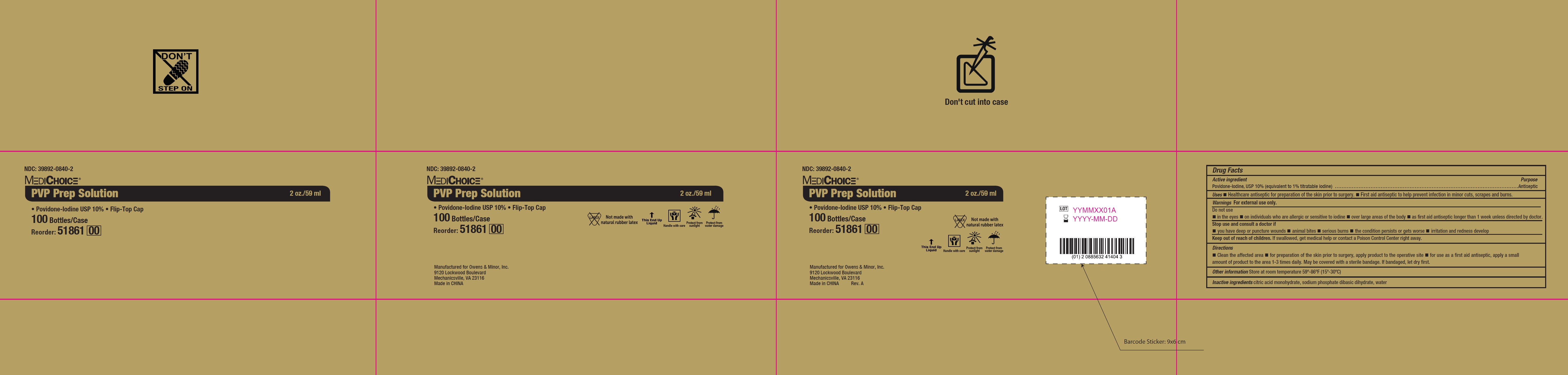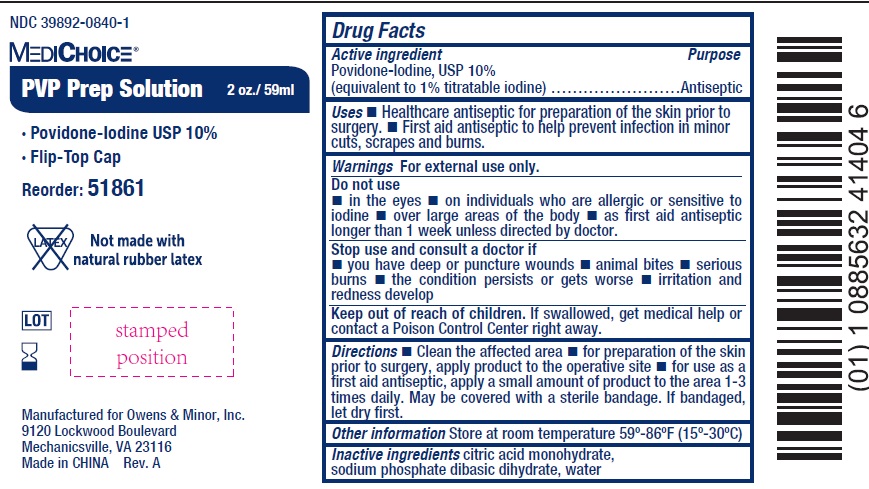 DRUG LABEL: MediChoice PVP Prep
NDC: 39892-0840 | Form: SOLUTION
Manufacturer: O&M HALYARD, INC.
Category: otc | Type: HUMAN OTC DRUG LABEL
Date: 20251009

ACTIVE INGREDIENTS: POVIDONE-IODINE 100 mg/1 mL
INACTIVE INGREDIENTS: CITRIC ACID MONOHYDRATE; SODIUM PHOSPHATE, DIBASIC, DIHYDRATE; WATER

MediChoice PVP Prep Solution

Active ingredient

Povidone-Iodine, USP 10% (equivalent to 1% titratable iodine)

Purpose

Antiseptic

Uses

- Healthcare antiseptic for preparation of the skin prior to surgery.
- First aid antiseptic to help prevent infection in minor cuts, scrapes and burns.

Warnings

For external use only.

Do not use

- in the eyes
- on individuals who are allergic or sensitive to iodine
- over large areas of the body
- as first aid antiseptic longer than 1 week unless directed by doctor.

Stop use and consult a doctor if

- you have deep or puncture wounds
- animal bites
- serious burns
- the condition persists or gets worse
- irritation and redness develop

Keep out of reach of children.

If swallowed, get medical help or contact a Poison Control Center right away.

Directions

- Clean the affected area
- for preparation of the skin prior to surgery, apply product to the operative site
- for use as a first aid antiseptic, apply a small amount of product to the area 1-3 times daily. May be covered with a sterile bandage. If bandaged, let dry first.

Other information

Store at room temperature 59º-86ºF (15º-30ºC)

Inactive ingredients

citric acid monohydrate, sodium phosphate dibasic dihydrate, water